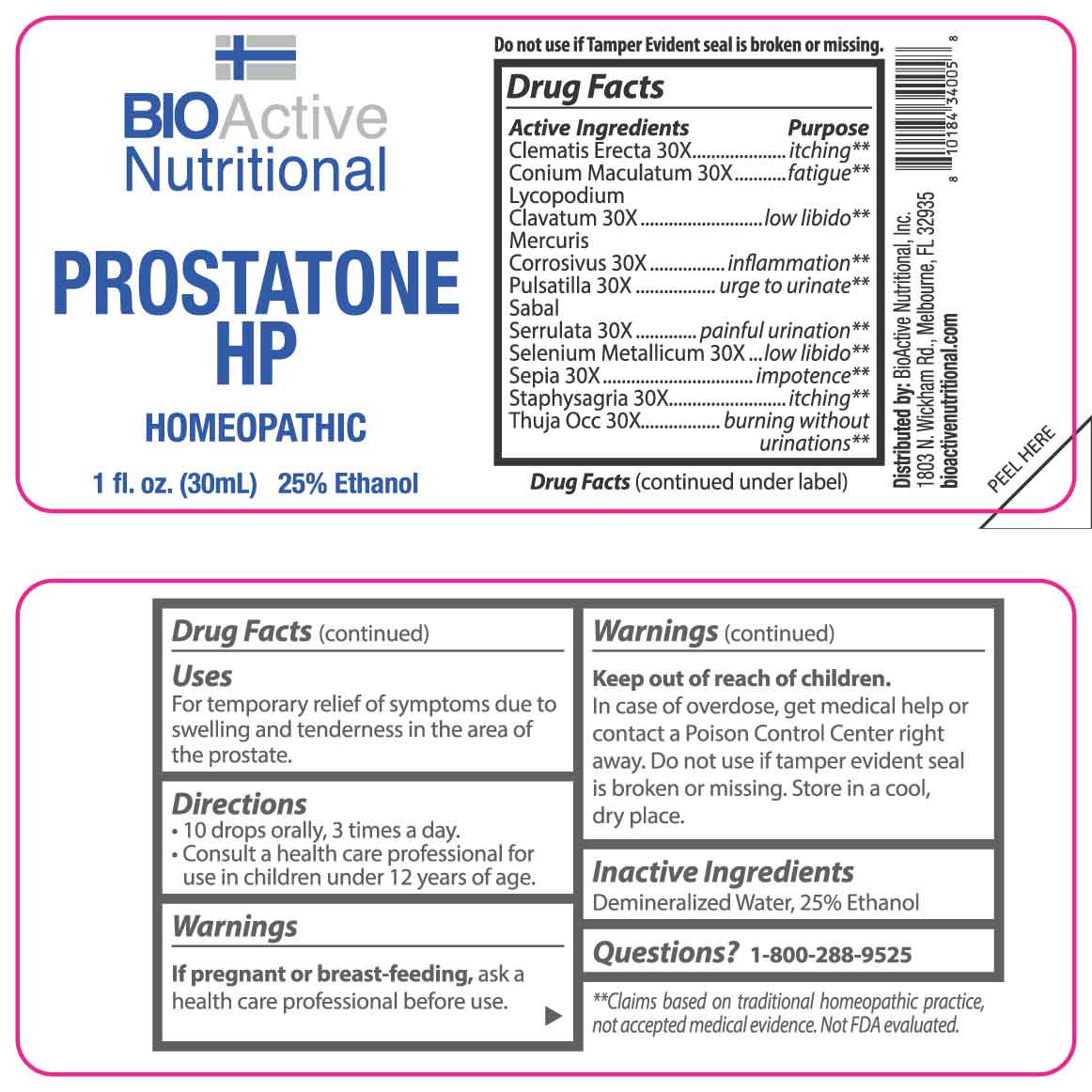 DRUG LABEL: Prostatone
NDC: 43857-0392 | Form: LIQUID
Manufacturer: BioActive Nutritional, Inc
Category: homeopathic | Type: HUMAN OTC DRUG LABEL
Date: 20250402

ACTIVE INGREDIENTS: CLEMATIS RECTA FLOWERING TOP 30 [hp_X]/1 mL; CONIUM MACULATUM FLOWERING TOP 30 [hp_X]/1 mL; LYCOPODIUM CLAVATUM SPORE 30 [hp_X]/1 mL; MERCURIC CHLORIDE 30 [hp_X]/1 mL; PULSATILLA VULGARIS 30 [hp_X]/1 mL; SAW PALMETTO 30 [hp_X]/1 mL; SELENIUM 30 [hp_X]/1 mL; SEPIA OFFICINALIS JUICE 30 [hp_X]/1 mL; DELPHINIUM STAPHISAGRIA SEED 30 [hp_X]/1 mL; THUJA OCCIDENTALIS LEAFY TWIG 30 [hp_X]/1 mL
INACTIVE INGREDIENTS: WATER; ALCOHOL

DRUG FACTS:

ACTIVE INGREDIENTS:

Clematis Erecta 30X, Conium Maculatum 30X, Lycopodium Clavatum 30X, Mercurius Corrosivus 30X, Pulsatilla 30X, Sabal Serrulata 30X, Selenium Metallicum 30X, Sepia 30X, Staphysagria 30X, Thuja Occidentalis 30X.

PURPOSE:

Clematis Erecta - itching,** Conium Maculatum - fatigue,** Lycopodium Clavatum – low libido,** Mercurius Corrosivus - inflammation,** Pulsatilla – urge to urinate,** Sabal Serrulata – painful urination,** Selenium Metallicum – low libido,** Sepia - impotence,** Staphysagria - itching,** Thuja Occidentalis – burning without urinations**
**Claims based on traditional homeopathic practice, not accepted medical evidence. Not FDA evaluated.

USES:

For temporary relief of symptoms due to swelling and tenderness in the area of the prostate.

WARNINGS:

If pregnant or breast-feeding, ask a health care professional before use.

Keep out of reach of children. In case of overdose, get medical help or contact a Poison Control Center right away.

Do not use if tamper evident seal is broken or missing.

Store in a cool, dry place.

KEEP OUT OF REACH OF CHILDREN:

In case of overdose, get medical help or contact a Poison Control Center right away.

DIRECTIONS:

• 10 drops orally, 3 times a day.

• Consult a health care professional for use in children under 12 years of age.

INACTIVE INGREDIENTS:

Demineralized water, 25% Ethanol

QUESTIONS:

Distributed by:
BioActive Nutritional, Inc.
1803 N. Wickham Rd.
Melbourne, FL 32935
bioactivenutritional.com

1-800-288-9525

PACKAGE LABEL DISPLAY:

BIOActive Nutritional

PROSTATONE HP

HOMEOPATHIC

1 FL OZ (30 ml)